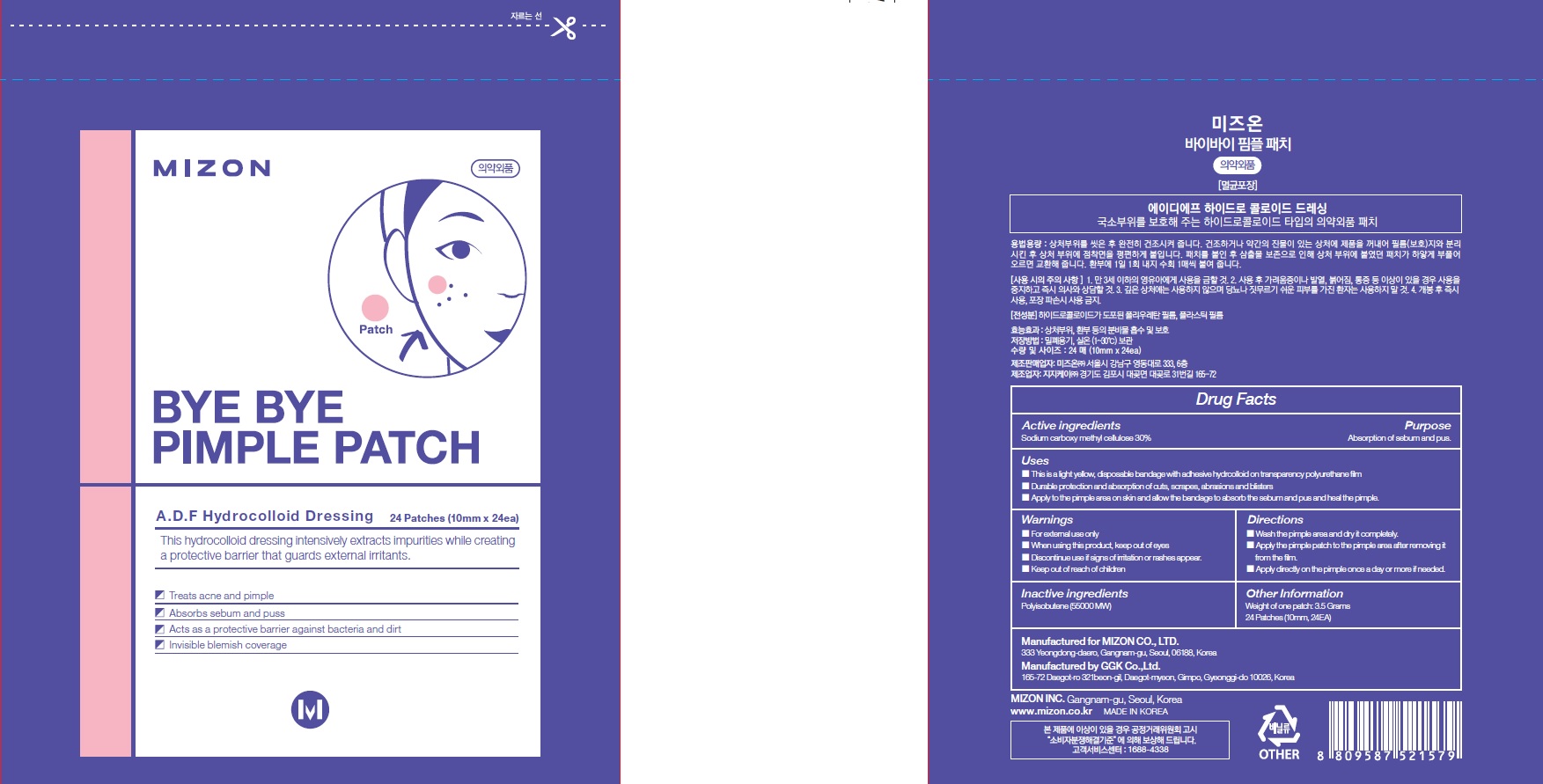 DRUG LABEL: Mizon Bye Bye Pimple
NDC: 57718-200 | Form: PATCH
Manufacturer: MIZON CO.,LTD.
Category: otc | Type: HUMAN OTC DRUG LABEL
Date: 20180608

ACTIVE INGREDIENTS: CARBOXYMETHYLCELLULOSE 1.05 g/3.5 g
INACTIVE INGREDIENTS: POLYISOBUTYLENE (55000 MW)

ACTIVE INGREDIENT

Active ingredients: Sodium carboxymethyl cellulose 30%

INACTIVE INGREDIENT

Inactive ingredients:

POLYISOBUTYLENE (55000 MW)

PURPOSE

Purpose: Absorption of sebum and pus

WARNINGS

- For external use only

- When using this product, keep out of eyes

- Discontinue use if signs of irritation or rashes appear.

- Keep out of reach of children

KEEP OUT OF REACH OF CHILDREN

Uses

- This is a light yellow, disposable bandage with adhesive hydrcolloid on transparency polyurethane film.

- Durable protection and absorption of cuts, scrapes, abrasions and blisters.

- Apply to the pimple area on skin and allow the bandage to absorb the sebum and pus and heal the pimple.

Directions

- Wash the pimple area and dry it completely.

- Apply the pimple patch to the pimple area after removing it from the film.

- Apply directly on the pimple once a day or more if needed.